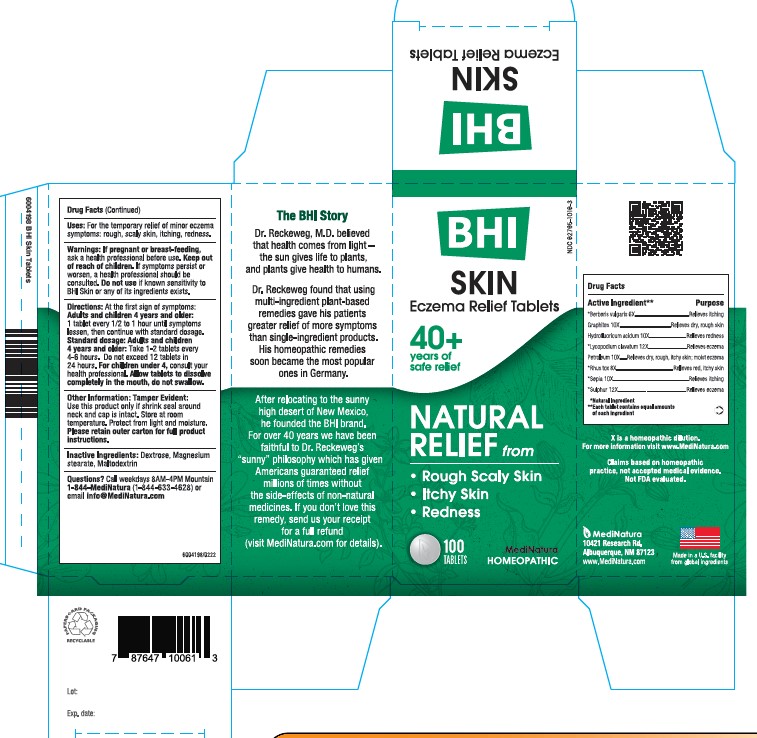 DRUG LABEL: BHI Skin
NDC: 62795-1016 | Form: TABLET
Manufacturer: MediNatura Inc
Category: homeopathic | Type: HUMAN OTC DRUG LABEL
Date: 20220707

ACTIVE INGREDIENTS: BERBERIS VULGARIS ROOT BARK 6 [hp_X]/1 1; GRAPHITE 10 [hp_X]/1 1; HYDROFLUORIC ACID 10 [hp_X]/1 1; LYCOPODIUM CLAVATUM SPORE 12 [hp_X]/1 1; PETROLATUM 10 [hp_X]/1 1; TOXICODENDRON PUBESCENS LEAF 8 [hp_X]/1 1; SEPIA OFFICINALIS JUICE 10 [hp_X]/1 1; SULFUR 12 [hp_X]/1 1
INACTIVE INGREDIENTS: MAGNESIUM STEARATE; MALTODEXTRIN; DEXTROSE

BHI Skin Tablet

ACTIVE INGREDIENTS

Each tablet contains: *Berberis vulgaris 6X, Graphites 10X, Hydrofluoricum acidum 10X, *Lycopodium clavatum 12X, *Petroleum 10X, *Rhus toxicodendron 8X, *Sepia 10X, *Sulphur 12X 37.5 mg each.

*Natural Ingredients

INACTIVE INGREDIENTS

Inactive Ingredients: Dextrose, Magnesium Stearate, Maltodextrin

PURPOSE

Eczema Relief Tablets

Relieves:

• Rough Scaly Skin

• Itching Skin

• Redness

USES

For the temporary relief of minor eczema symptoms: rough scaly skin, itching skin, redness

Directions

At first sign of symptoms: Adults and children 4 years and older: 1 tablet every 1/2 to 1 hour until symptoms lessen, then continue with standard dosage.

Standard dosage: Adults and children 4 years and older: Take 1-2 tablet every 4 to 6 hours. Do not exceed 12 tablets in 24 hours.For children under 4, consult your health professional.

Allow tablets to dissolve completely in the mouth, do not swallow.

WARNINGS SECTION

If pregnant or breast-feeding, ask a health professional before use. Keep out of reach of children. If symptoms persist or worsen, a health professional should be consulted. Do not use if known sensitivity to BHI Skin or any of its ingredients exists.

KEEP OUT OF REACH OF CHILDREN

PACKAGE LABEL

Add image transcription here...